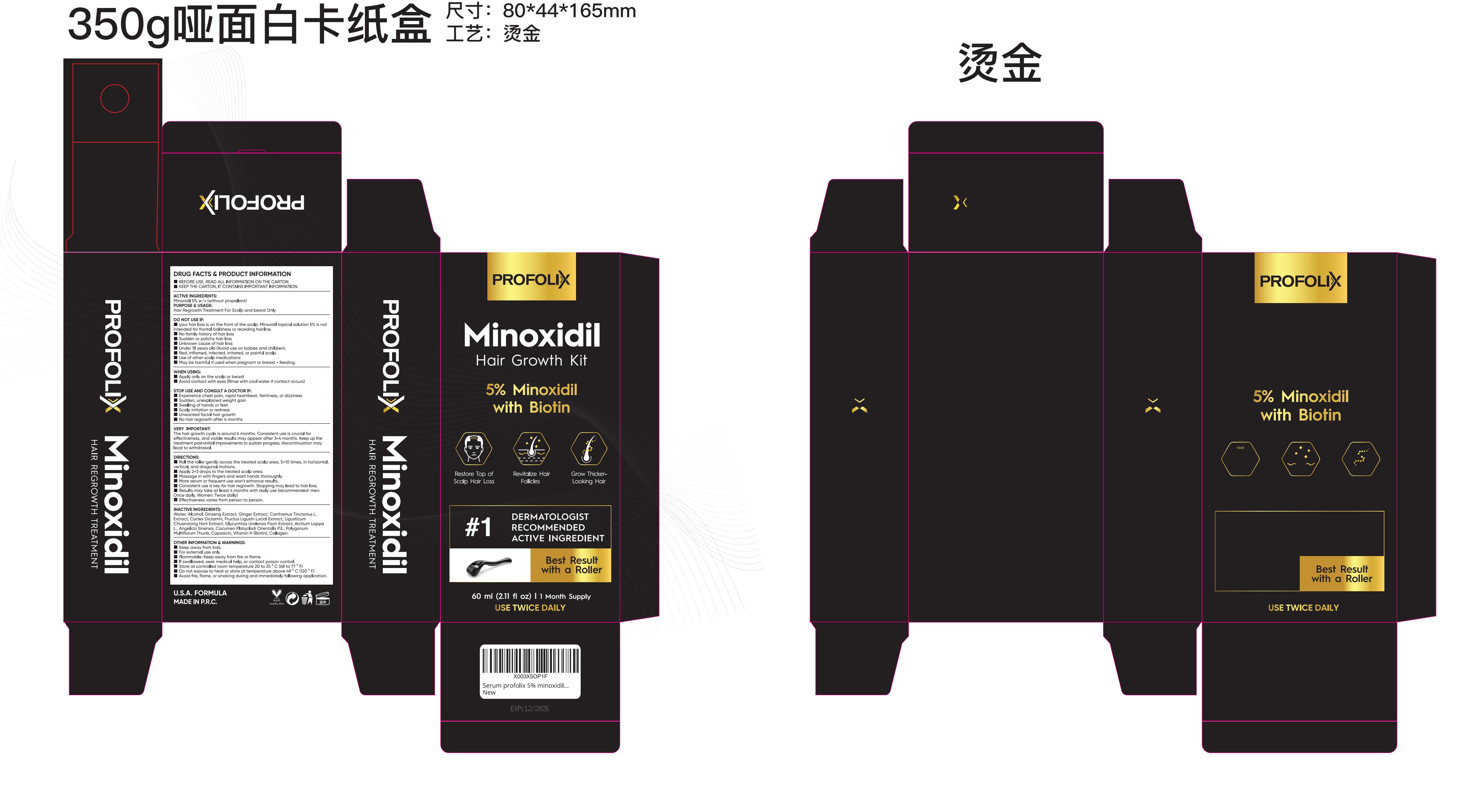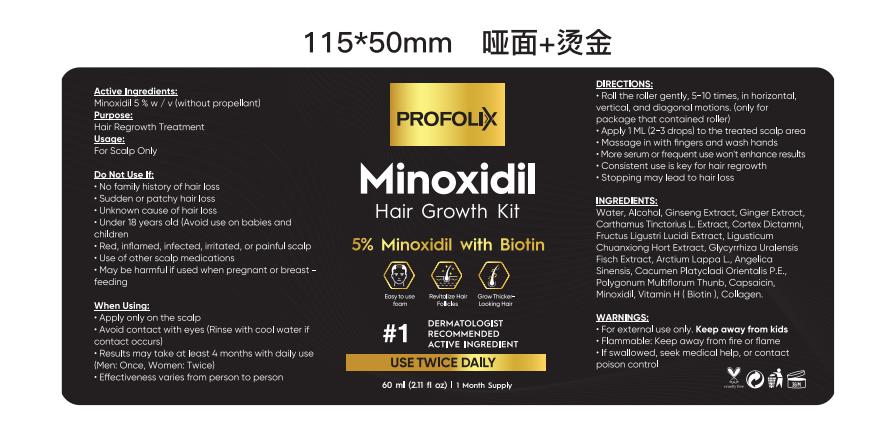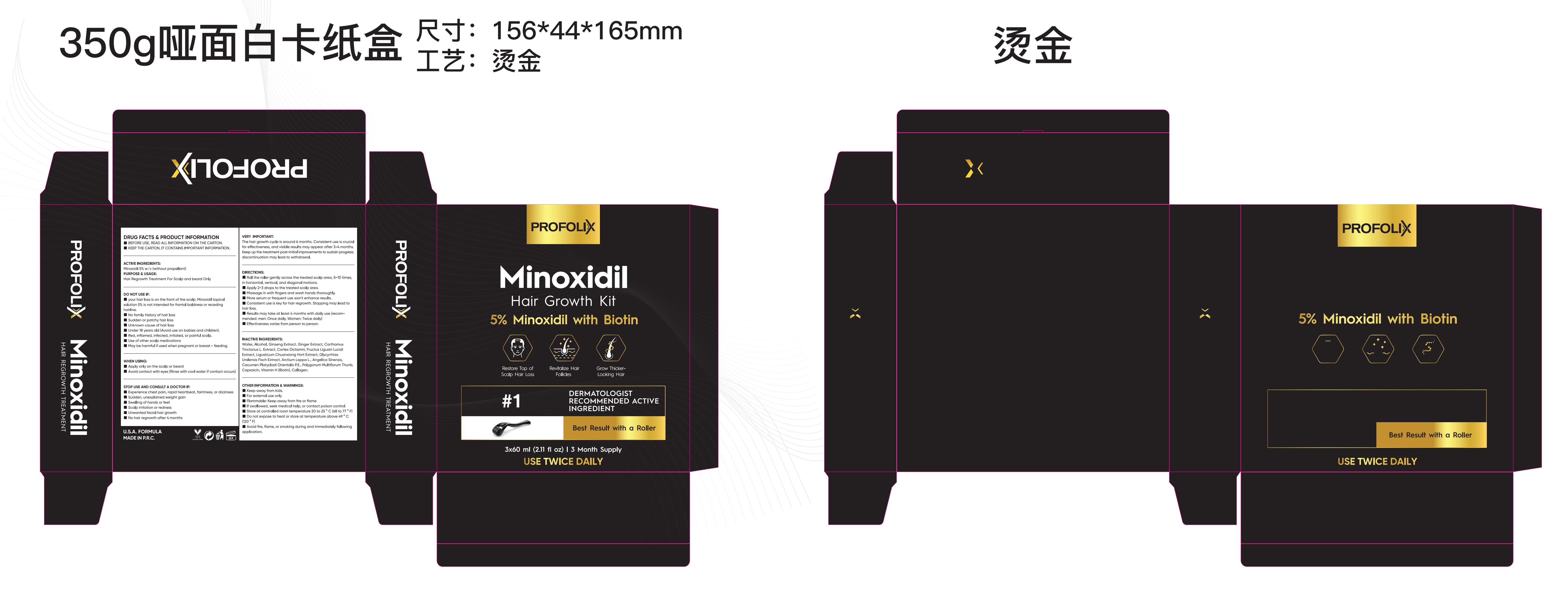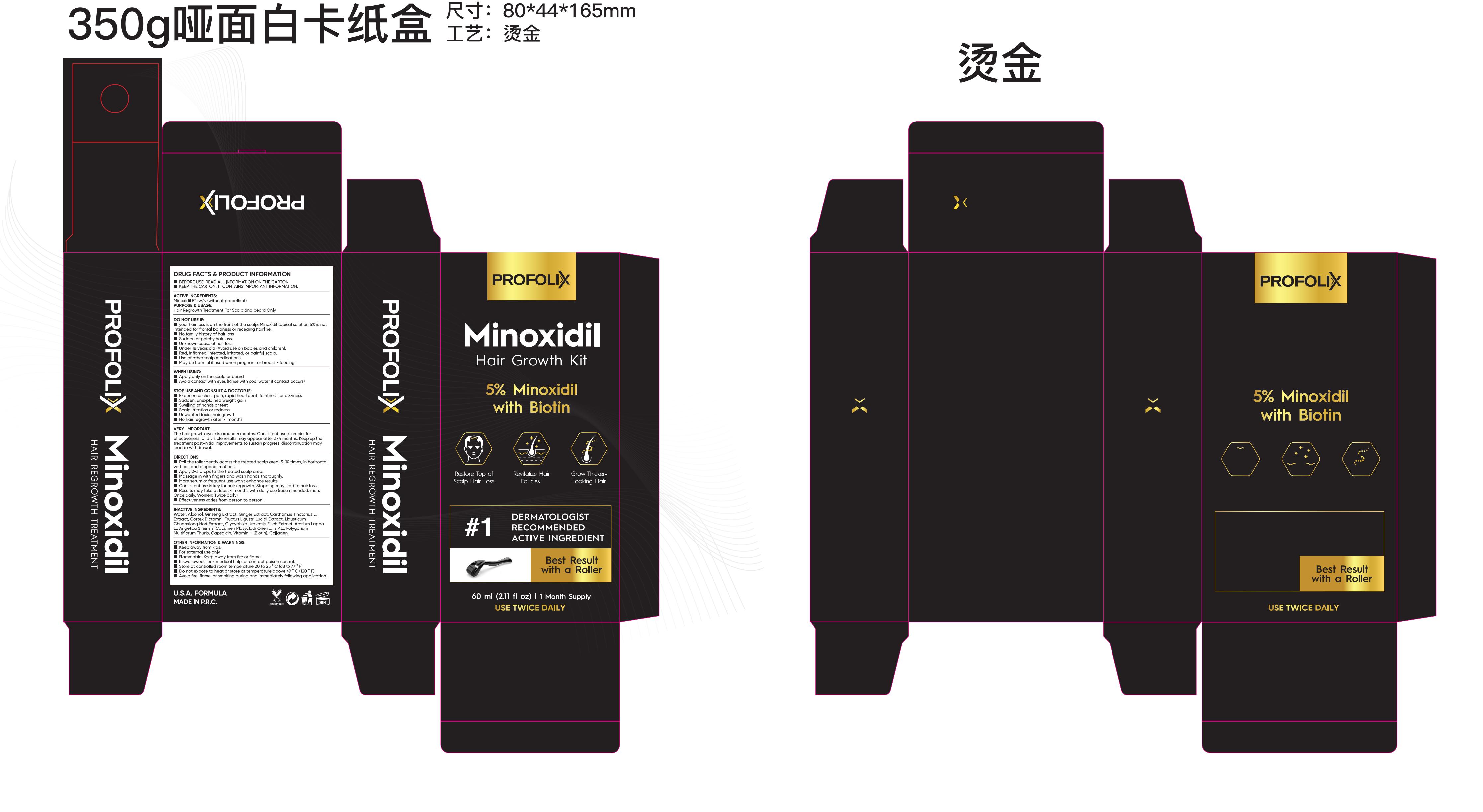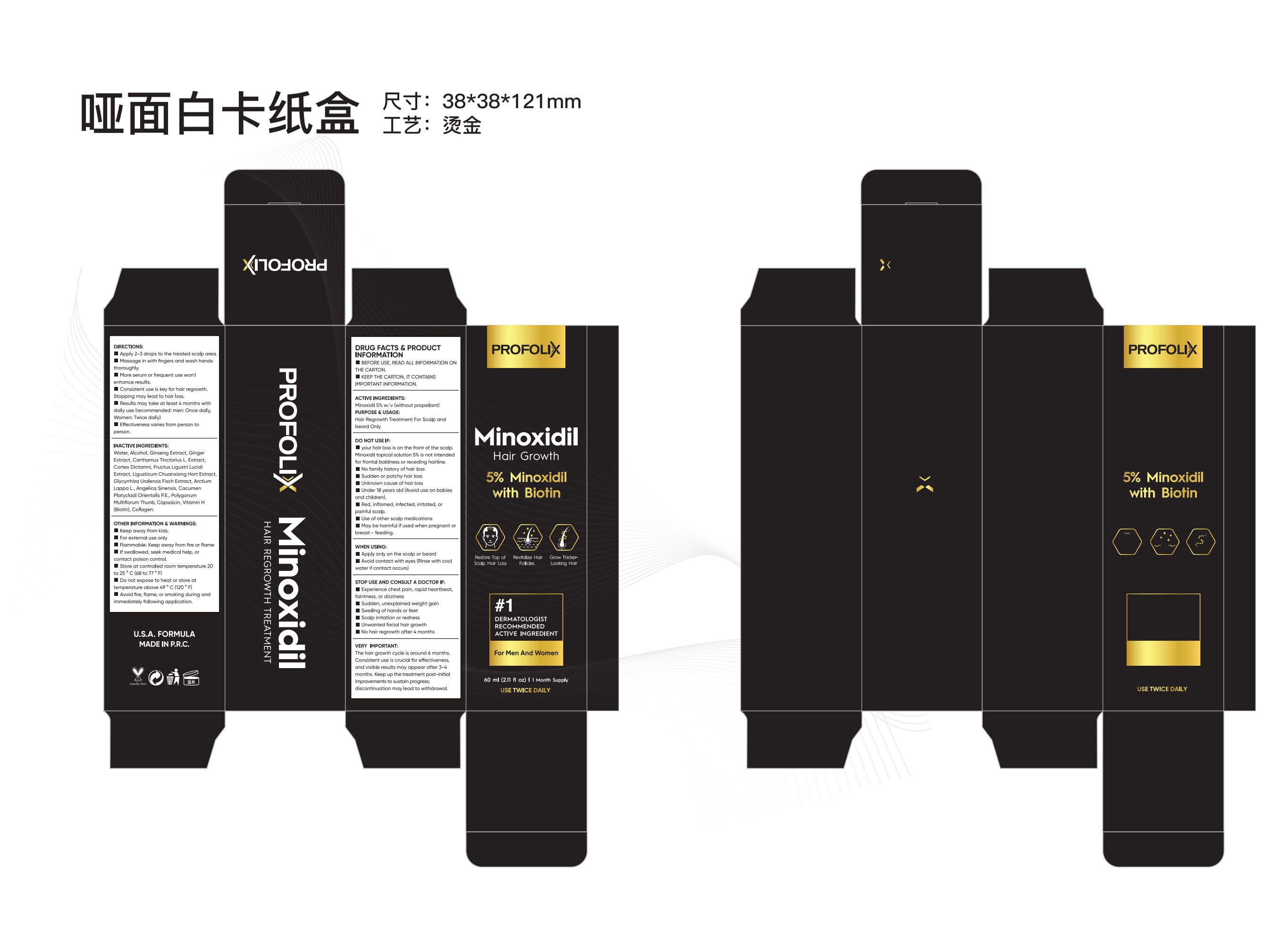 DRUG LABEL: PROFOLIX MINOXIDIL HAIR GROWTH SERUM
NDC: 81653-009 | Form: LIQUID
Manufacturer: Guangzhou Jianyuan Biological Technology.Co.,Ltd
Category: otc | Type: HUMAN OTC DRUG LABEL
Date: 20231128

ACTIVE INGREDIENTS: MINOXIDIL 5 g/100 mL
INACTIVE INGREDIENTS: CARTHAMUS TINCTORIUS WHOLE; LIGUSTICUM WALLICHII ROOT; GLYCYRRHIZA URALENSIS WHOLE; CAPSAICIN; BIOTIN; DICTAMNUS DASYCARPUS ROOT; ALCOHOL; ARCTIUM LAPPA WHOLE; HOODIA GORDONII SAP; WATER; GINGER; ANGELICA SINENSIS ROOT; REYNOUTRIA MULTIFLORA STEM; ASIAN GINSENG; LIGUSTRUM LUCIDUM FRUIT; COLLAGEN ALPHA-1(I) CHAIN BOVINE

81653-009

Active Ingredient

Minoxidil 5% w/v (without propellant)

Purpose

Hair Regrowth Treatment For Scalp and beard Only

Use

To Regrow hair, For Scalp and beard Only

Warnings

Keep away from kids.
for external use only
Flammable: Keep away from fire or flame
If swallowed, seek medical help, or contact poison control.
Store at controlled room temperature 20 to 25 ° C (68 to 77 ° F)
Do not expose to heat or store at temperature above 49 ° C (120 ° F)
Avoid fire, flame, or smoking during and immediately following application.

Do not use

your hair loss is on the front of the scalp. Minoxidil topical solution 5% is not intended for frontal baldness or receding hairline.
No family history of hair loss
Sudden or patchy hair loss
Unknown cause of hair loss
Under 18 years old (Avoid use on babies and children).
Red, inflamed, infected, irritated, or painful scalp.
Use of other scalp medications
May be harmful if used when pregnant or breast - feeding.

When Using

Apply only on the scalp or beard
Avoid contact with eyes (Rinse with cool water if contact occurs)

Stop Use

Experience chest pain, rapid heartbeat, faintness, or dizziness
Sudden, unexplained weight gain
Swelling of hands or feet
Scalp irritation or redness
Unwanted facial hair growth
No hair regrowth after 4 months

Ask Doctor

If have Allergy, plz check with doctor

Keep Oot Of Reach Of Children

Directions

Roll the roller gently across the treated scalp area, 5-10 times, in horizontal, vertical, and diagonal motions.
Apply 2-3 drops to the treated scalp area.
Massage in with fingers and wash hands thoroughly.
More serum or frequent use won't enhance results.
Consistent use is key for hair regrowth. Stopping may lead to hair loss.
Results may take at least 4 months with daily use (recommended: men: Once daily, Women: Twice daily)
Effectiveness varies from person to person.

IMPORTANT

The hair growth cycle is around 6 months. Consistent use is crucial for effectiveness, and visible results may appear after 3-4 months. Keep up the treatment post-initial improvements to sustain progress; discontinuation may lead to withdrawal.

Inactive ingredients

Water, Alcohol, Ginseng Extract, Ginger Extract, Carthamus Tinctorius L. Extract, Cortex Dictamni, Fructus Ligustri Lucidi Extract, Ligusticum Chuanxiong Hort Extract, Glycyrrhiza Uralensis Fisch Extract, Arctium Lappa L., Angelica Sinensis, Cacumen Platycladi Orientalis P.E., Polygonum Multiflorum Thunb, Capsaicin, Vitamin H (Biotin), Collagen.